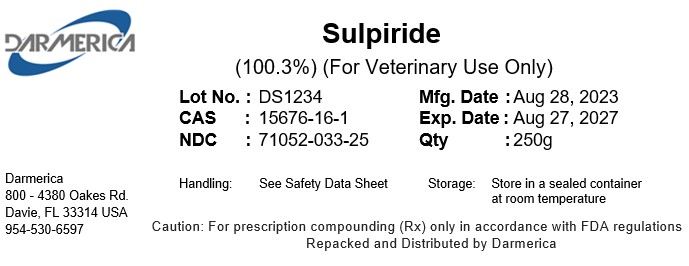 DRUG LABEL: Sulpiride
NDC: 71052-033 | Form: POWDER
Manufacturer: DARMERICA, LLC
Category: other | Type: BULK INGREDIENT - ANIMAL DRUG
Date: 20260105

ACTIVE INGREDIENTS: SULPIRIDE 1 g/1 g

Sulpiride